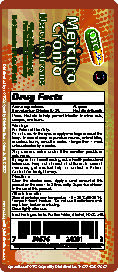 DRUG LABEL: Mercurochrome
NDC: 69469-013 | Form: SOLUTION
Manufacturer: Vitamin USA, Corp
Category: otc | Type: HUMAN OTC DRUG LABEL
Date: 20240905

ACTIVE INGREDIENTS: BENZALKONIUM CHLORIDE 1.3 mg/1 mL
INACTIVE INGREDIENTS: WATER; ALCOHOL; FD&C RED NO. 40

MercuroChrome 1oz

Active Ingredient

Active Ingredients: Purpose

Benzalkoinum Chloride 0.13% First Aid Antiseptic

Uses

Uses: First aid to help prevent infection in minor cuts, scrapes, and burns.

Warnings:

For External Use Only

Do Not Use: in the eyes or apply over large areas of the body. In case of deep or puncture wounds, animal bites, or serious burns, consult a doctor. Longer than 1 week unless directed by doctor.

Stop use and ask a doctor if the condition perssits or gets worse.

If pregannt or breastfeeding

If pregnant or breastfeeding, ask a health professional before use. Keep out of reach of children. In case of overdose, get medical help or contact a Poison Control Center right away.

Directions

Clean the affected area. Apply small amount of this product on the area 1 to 3 times daily. Supervise children in the use of this product.

Other Information

Store at controlled room temperature: 15-30°C (59-86°F). Tamper Evident Feature: Do not use if cello-band over cap is torn, broken or missing. Close tightly after use.

Inactive ingredients

Inactive ingredients: Purified Water, Alcohol, FD&C #40

Directions

Clean the affected area. Apply small amount of this product on the area 1 to 3 times daily. Supervise children in the use of this product.

Keep out of reach of children

If pregnant or breastfeeding, ask a health professional before use. Keep out of reach of children. In case of overdose, get medical help or contact a Poison Control Center right away.

PACKAGE LABEL

Mercuro

Cromo

Mercurochrome

First Aid Antiseptic

For External Use Only

Net Contents: 1 Fl Oz. (30 mL)